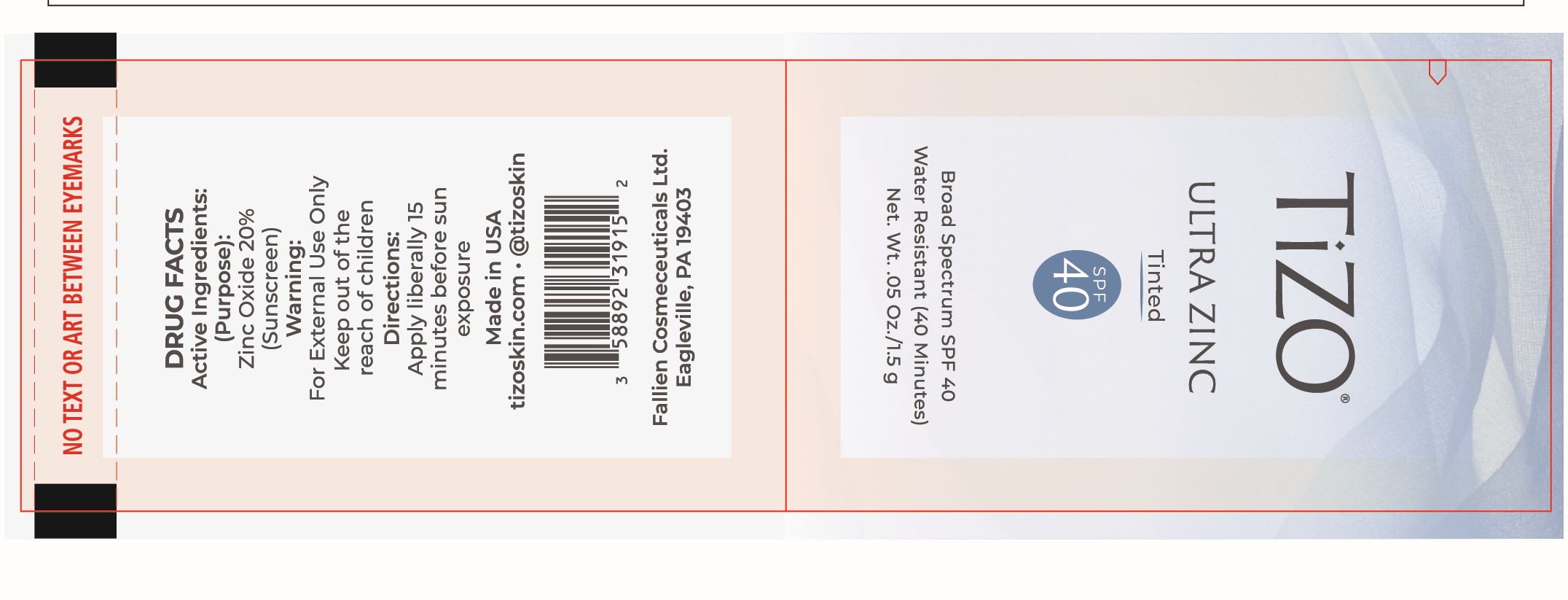 DRUG LABEL: TiZO Ultra Zinc SPF 40 (Tinted)
NDC: 58892-319 | Form: CREAM
Manufacturer: Fallien Cosmeceuticals, LTD
Category: otc | Type: HUMAN OTC DRUG LABEL
Date: 20250131

ACTIVE INGREDIENTS: ZINC OXIDE 200 mg/1 g
INACTIVE INGREDIENTS: C12-15 ALKYL BENZOATE; CAPRYLHYDROXAMIC ACID; IRON OXIDES; TRIETHANOLAMINE; CYCLOHEXASILOXANE; PEG-10 DIMETHICONE (600 CST); BISMUTH OXYCHLORIDE; CAPRYLYL GLYCOL; POLYGLYCERYL-4 ISOSTEARATE; POLYHYDROXYSTEARIC ACID (2300 MW); STEARYL DIMETHICONE (400 MPA.S AT 50C); MICROCRYSTALLINE WAX; POLYSORBATE 20; TETRAHEXYLDECYL ASCORBATE; ALPHA-TOCOPHEROL ACETATE; MICA; PEG-30 DIPOLYHYDROXYSTEARATE; TRIETHOXYCAPRYLYLSILANE; WATER; CETYL PEG/PPG-10/1 DIMETHICONE (HLB 4); SODIUM CHLORIDE; DIMETHICONE/VINYL DIMETHICONE CROSSPOLYMER (SOFT PARTICLE); CYCLOPENTASILOXANE; DIMETHICONE; DIMETHICONE CROSSPOLYMER; EDETATE DISODIUM ANHYDROUS; GLYCERIN; HYDROGEN DIMETHICONE (20 CST); DIMETHICONOL (2000 CST)

Active Ingredients:

Zinc Oxide 20%

Purpose:

Sunscreen

Directions:

Apply liberally 15 minutes before sun exposure.

Warnings:

For external use only. Keep out of the reach of children.

Warnings and Directions:

For external use only. Keep out of the reach of children. Apply liberally 15 minutes before suns exposure.

INACTIVE INGREDIENT

Bismuth Oxychloride, C12-15 Alkyl Benzoate, Caprylhydroxamic Acid, Caprylyl Glycol, Cetyl PEG/PPG-10/1 Dimethicone, Cyclohexasiloxane, Cyclopentasiloxane, Dimethicone, Dimethicone Crosspolymer, Dimethicone/Vinyl Dimethicone Crosspolymer, Dimethiconol, Disodium EDTA, Glycerin, Hydrogen Dimethicone, Iron Oxides, Mica, Microcrystalline Wax, PEG-10 Dimethicone, PEG-30 Dipolyhydroxystearate, Polyglyceryl-4 Isostearate, Polyhydroxystearic Acid, Polysorbate 20, Sodium Chloride, Stearyl Dimethicone, Tetrahexyldecyl Ascorbate, Tocopheryl Acetate, Triethanolamine, Triethoxycaprylylsilane, Water

Warning:

Keep out of the reach of children.